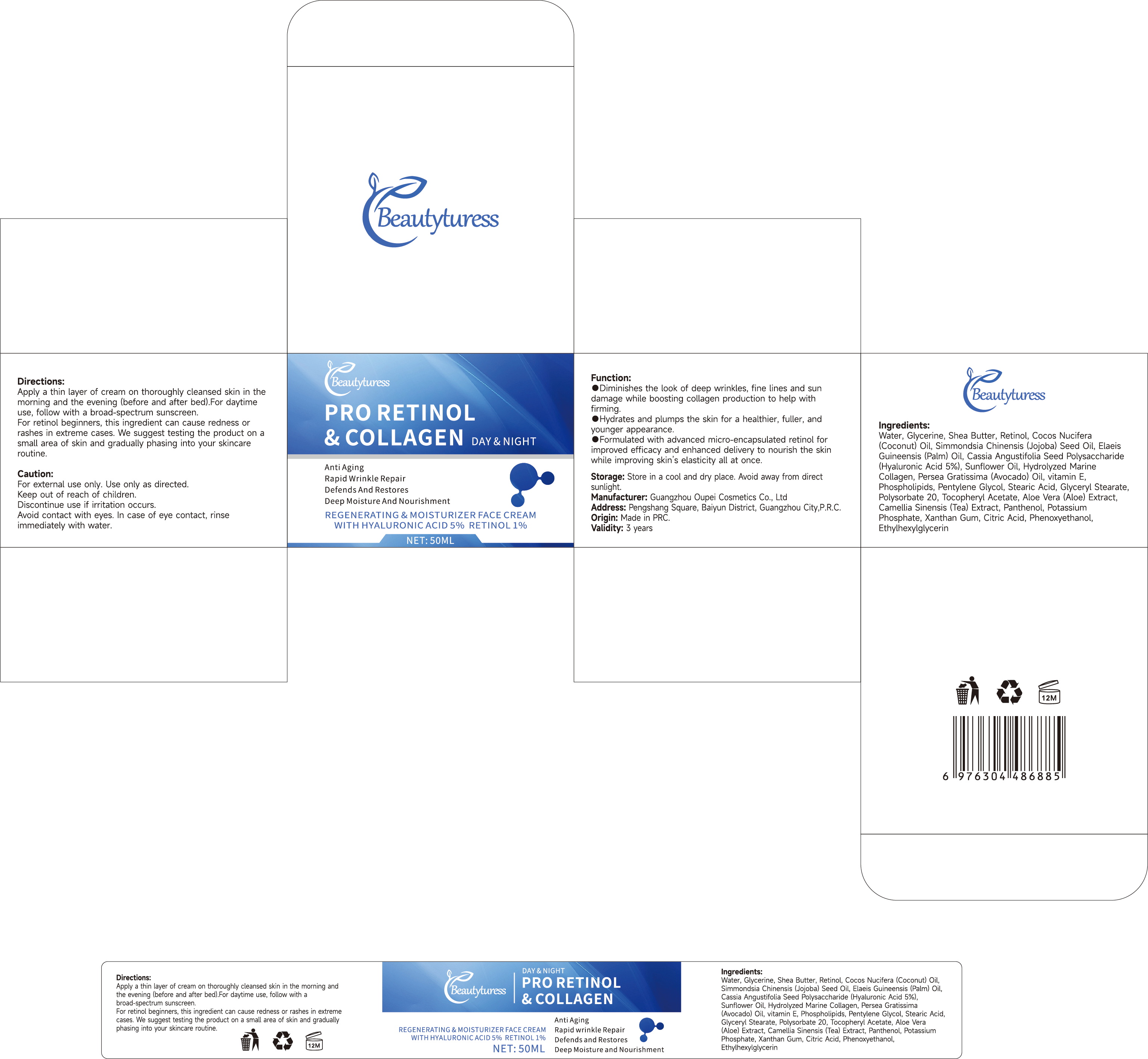 DRUG LABEL: Beautyturess Retinol Cream
NDC: 84753-004 | Form: EMULSION
Manufacturer: Guangdong Bisutang Biotechnology Co., Ltd.
Category: otc | Type: HUMAN OTC DRUG LABEL
Date: 20241009

ACTIVE INGREDIENTS: RETINYL RETINOATE 0.099 g/50 g; ARBUTIN 0.005 g/50 g; NIACINAMIDE 0.005 g/50 g
INACTIVE INGREDIENTS: PHENOXYETHANOL; MINERAL OIL; GLYCERYL STEARATE SE; PETROLATUM; FRUCTOSE; STEARIC ACID; DIPROPYLENE GLYCOL; GLYCERIN; CARBOMER 1342; .ALPHA.-TOCOPHEROL; 1,2-HEXANEDIOL; 2'-HYDROXYACETOPHENONE; CUPRIC TRIETHANOLAMINE; PEG-100 STEARATE; CAPRYLIC/CAPRIC/LAURIC TRIGLYCERIDE; ETHYLHEXYLGLYCERIN; ACETYL HEXAPEPTIDE-8; WATER; CAPRYLYL GLYCOL

ACTIVE INGREDIENT

Retinyl Palmitate 0.198%
ARBUTIN 0.001%
NIACINAMIDE 0.001%

PURPOSE

After cleansing andtoning, take an appropriate amount ofthis product and apply it evenly on theface, massage until absorbed

Ask Doctor

If you have a history of skin allergies or have sensitive skin, it is advisable to consult a doctor before using this product.

DOSAGE AND ADMINISTRATION

Apply once daily to clean face and neck, avoiding the eye area

WHEN USING

Avoid contact with eyes and broken skin. If redness, swelling, or irritation occurs, discontinue use immediately and seek medical advice.

WARNINGS

Risk InformationFor external use only
Mention de risquesPour usage externe seulement
Do not use on damaged or broken skin.
Ne pas utiliser sur la peau endommagée ou avec des lésions
If rash occurs, discontinue use and consult a health care practitioner.
En présence d'une éruption cutanée, cesser l'utilisation et consulter un praticien de soins de santé
When using this product keep out of eyes. Rinse with water to remove.
Eviter tout contact avec les yeux. Rincer a l'eau le cas échéant
Keep out of reach of children. If swallowed, get medical help or contact a Poison Control Center right away.
Tenir hors de portée des enfants
En cas d'ingestion, consulter un médecin ou appeler un centre antipoison immédiatement.

INDICATIONS AND USAGE

Helps improve skin texture and tone, providing moisturization.

Keep out of reach of children. If swallowed, get medical help or contact a Poison Control Center right away.
Tenir hors de portée des enfants
En cas d'ingestion, consulter un médecin ou appeler un centre antipoison immédiatement.

INACTIVE INGREDIENT

PHENOXYETHANOL
MINERAL OIL
GLYCERYL STEARATE SE
PETROLATUM
FRUCTOSE
STEARIC ACID
DIPROPYLENE GLYCOL
GLYCERIN
CARBOMER 1342
ALPHA.-TOCOPHEROL
1.2-HEXANEDIOL
2'-HYDROXYACETOPHENONE
CUPRIC TRIETHANOLAMINE
PEG-100 STEARATE
CAPRYLIC/CAPRIC/LAURIC TRIGLYCERIDE
ETHYLHEXYLGLYCERIN
ACETYL HEXAPEPTIDE-8
WATER
CAPRYLYL GLYCOL